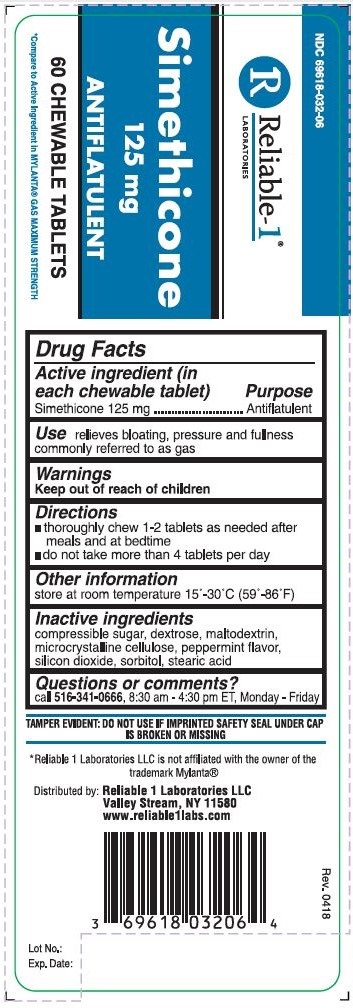 DRUG LABEL: Simethicone 125 mg
NDC: 69618-032 | Form: TABLET, CHEWABLE
Manufacturer: Reliable 1 Laboratires LLC
Category: otc | Type: HUMAN OTC DRUG LABEL
Date: 20250115

ACTIVE INGREDIENTS: DIMETHICONE 125 mg/1 1
INACTIVE INGREDIENTS: SUCROSE; MALTODEXTRIN; PEPPERMINT; SORBITOL; STEARIC ACID; DEXTROSE; CELLULOSE, MICROCRYSTALLINE; SILICON DIOXIDE

Simethicone 125 mg

Drug Facts

Active ingredient (in each chewable tablet)

Simethicone 125 mg

PURPOSE

Antiflatulent

Use

relieves bloating, pressure and fullness commonly referred to as gas

Warnings

Keep out of reach of children

Keep out of reach of children

Directions

- thoroughly chew 1-2 tablets as needed after meals and at bedtime
- do not take more than 4 tablets per day

Other information

store at room temperature 15°-30°C (59°-86°F)

Inactive ingredients

compressible sugar, dextrose, maltodextrin, microcrystaline cellulose, peppermint flavor, silicon dioxide, sorbitol, stearic acid

Questions or comments?

call 516-341-0666, 8:30 am -4:30 pm ET, Monday - Friday

TAMPER EVIDENT: DO NOT USE IF IMPRINTED SAFETY SEAL UNDER CAP IS BROKEN OR MISSING

*Reliable 1 Laboratories LLC is not affiliated with the owner of the trademark Mylanta®

Distributed by: Reliable 1 Laboratories LLC

Valley Stream, NY 11580

www.reliable1labs.com

PACKAGE LABEL

NDC 69618-032-06

Simethicone 125 mg

ANTIFLATULENT

60 CHEWABLE TABLETS

*Compare to Active Ingredient in MYLANTA® GAS MAXIMUM STRENGTH